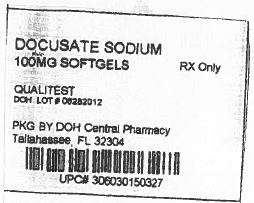 DRUG LABEL: DocQLace
NDC: 53808-0677 | Form: CAPSULE
Manufacturer: State of Florida DOH Central Pharmacy
Category: otc | Type: HUMAN OTC DRUG LABEL
Date: 20130910

ACTIVE INGREDIENTS: DOCUSATE SODIUM 100 mg/1 1
INACTIVE INGREDIENTS: FD&C RED NO. 40; FD&C YELLOW NO. 6; GELATIN; GLYCERIN; POLYETHYLENE GLYCOL 400; WATER; SORBITOL

DocQLace

Active ingredient (in each softgel)

Docusate sodium 100 mg

Purpose

Stool softener

Uses

- relieves occasional constipation (irregularity)
- generally produces bowel movement in 12 to 72 hours

Do not use if you are presently taking mineral oil, unless told to do so by a doctor

Ask a doctor before use if you have

- stomach pain
- nausea
- vomiting
- noticed a sudden change in bowel habits that lasts over 2 weeks

Stop use and ask a doctor if

- you have rectal bleeding or fail to have a bowel movement after use of a laxative. These could be signs of a serious condition.
- you need to use a laxative for more than 1 week

PREGNANCY OR BREAST FEEDING

If pregnant or breast-feeding, ask a health professional before use.

Keep out of reach of children.

In case of overdose, get medical help or contact a Poison Control Center right away.

Directions

doses may be taken as a single daily dose or in divided doses

adults and children 12 years and over | take 1-3 softgels daily
children 2 to under 12 years of age | take 1 softgel daily
children under 2 years | ask a doctor

Other information

- each softgel contains: sodium 5 mg VERY LOW SODIUM
- store at 15°-30°C (59°-86°F)
- keep tightly closed

You may report serious side effects to: 130 Vintage Drive, Huntsville, AL 35811.

Inactive ingredients

FD&C Red #40, FD&C Yellow #6, gelatin, glycerin, polyethylene glycol 400, purified water, sorbital special

Manufactured for:
QUALITEST PHARMACEUTICALS
HUNTSVILLE, AL 35811

They are supplied by State of Florida DOH Central Pharmacy as follows:

NDC | Strength | Quantity/Form | Color | Source Prod. Code
53808-0677-1 | 100 mg | 30 Capsules in a Blister Pack | Reddish | 0603-0150